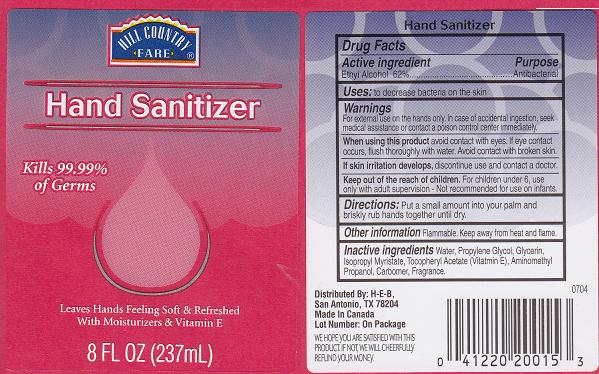 DRUG LABEL: HAND SANITIZER
NDC: 37808-225 | Form: GEL
Manufacturer: HEB
Category: otc | Type: HUMAN OTC DRUG LABEL
Date: 20100705

ACTIVE INGREDIENTS: ALCOHOL 62.0000 mL/100 mL

BACK LABEL - DRUG FACTS BOX

ACTIVE INGREDIENT

ETHYL ALCOHOL 62% (ANTISEPTIC)

USES AND DIRECTIONS

- USES: TO HELP REDUCE BACTERIA ON THE SKIN.
- DIRECTIONS: PUT A SMALL AMOUNT INTO YOUR PALM AND BRISKLY RUB HANDS TOGETHER UNTIL DRY.

WARNINGS

- FOR EXTERNAL USE ONLY.IN CASE OF ACCIDENTAL INGESTION, SEEK MEDICAL ASSISTANCE OR CONTACT A POISON CONTROL CENTER IMMEDIATELY.

WHEN USING THIS PRODUCT

AVOID CONTACT WITH EYES. IF CONTACT OCCURS, RINSE WITH WATER. AVOID CONTACT WITH BROKEN SKIN.

STOP USE AND ASK A DOCTOR IF

SKIN IRRITATION OR REDNESS DEVELOPS.

KEEP OUT OF REACH OF CHILDREN

FOR CHILDREN UNDER 6, USE ONLY WITH ADULT SUPERVISION. NOT RECOMMENDED FOR USE ON INFANTS.

OTHER INFORMATION

FLAMMABLE. KEEP AWAY FROM HEAT AND FLAME.

PACKAGE FRONT AND BACK LABELS

- 8OZ FRONT AND BACK LABELS: HCF8OZ.jpg